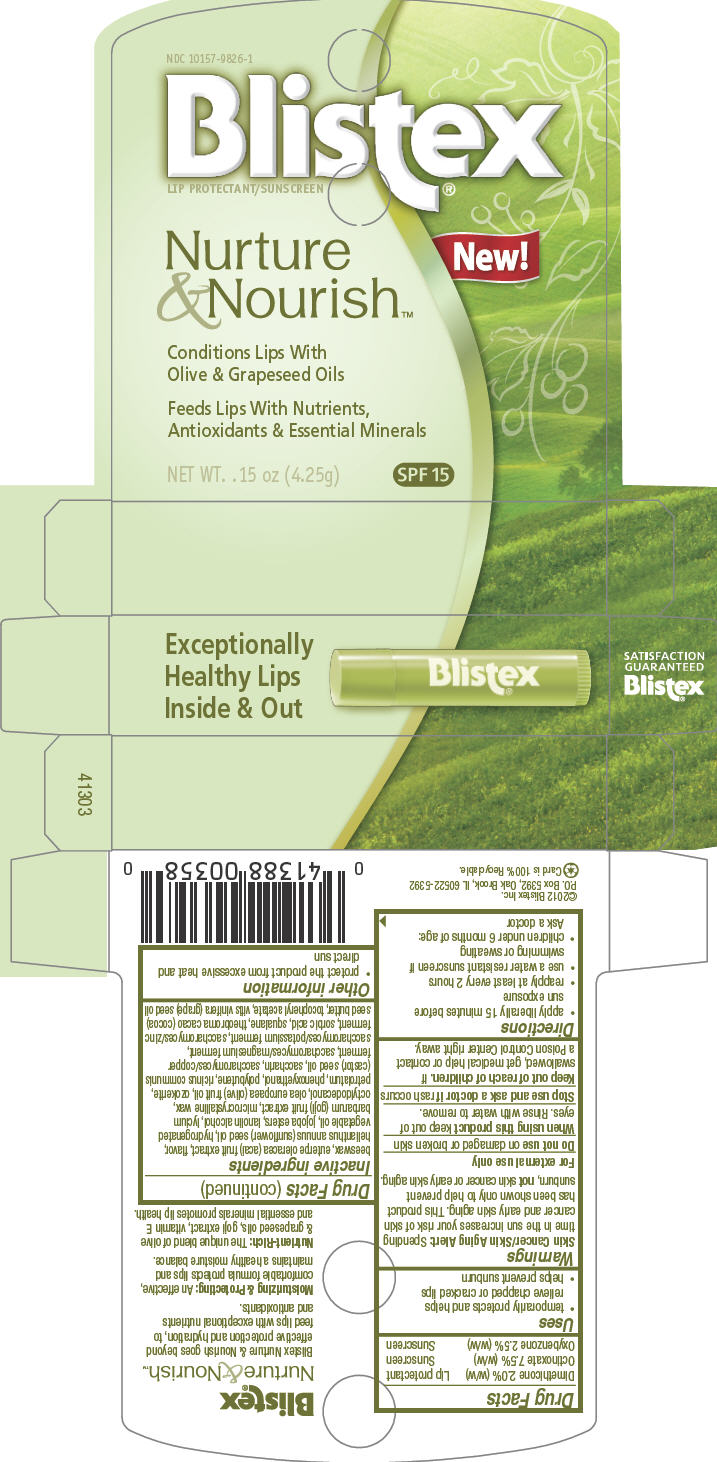 DRUG LABEL: Blistex 
NDC: 10157-9826 | Form: STICK
Manufacturer: Blistex Inc.
Category: otc | Type: HUMAN OTC DRUG LABEL
Date: 20130325

ACTIVE INGREDIENTS: Octinoxate 7.5 g/100 g; Oxybenzone 2.5 g/100 g; Dimethicone 2 g/100 g
INACTIVE INGREDIENTS: yellow wax; acai; sunflower oil; lanolin alcohols; lycium barbarum fruit; microcrystalline wax; octyldodecanol; olive oil; petrolatum; phenoxyethanol; castor oil; saccharin; sorbic acid; squalane; cocoa butter; .alpha.-tocopherol acetate; grape seed oil; ceresin

Blistex®
Nurture & Nourish

Drug Facts

ACTIVE INGREDIENT

PURPOSE

Dimethicone 2.0% (w/w) | Lip protectant
Octinoxate 7.5% (w/w) | Sunscreen
Oxybenzone 2.5% (w/w) | Sunscreen

Uses

- temporarily protects and helps relieve chapped or cracked lips
- helps prevent sunburn

Warnings

Skin Cancer/Skin Aging Alert

Spending time in the sun increases your risk of skin cancer and early skin aging. This product has been shown only to help prevent sunburn, not skin cancer or early skin aging.

For external use only

Do not use on damaged or broken skin

When using this product keep out of eyes. Rinse with water to remove.

Stop use and ask a doctor if rash occurs

Keep out of reach of children. If swallowed, get medical help or contact a Poison Control Center right away.

Directions

- apply liberally 15 minutes before sun exposure
- reapply at least every 2 hours
- use a water resistant sunscreen if swimming or sweating
- children under 6 months of age: Ask a doctor

Inactive ingredients

beeswax, euterpe oleracea (acai) fruit extract, flavor, helianthus annuus (sunflower) seed oil, hydrogenated vegetable oil, jojoba esters, lanolin alcohol, lycium barbarum (goji) fruit extract, microcrystalline wax, octyldodecanol, olea europaea (olive) fruit oil, ozokerite, petrolatum, phenoxyethanol, polybutene, ricinus communis (castor) seed oil, saccharin, saccharomyces/copper ferment, saccharomyces/magnesium ferment, saccharomyces/potassium ferment, saccharomyces/zinc ferment, sorbic acid, squalane, theobroma cacao (cocoa) seed butter, tocopheryl acetate, vitis vinifera (grape) seed oil

Other information

- protect the product from excessive heat and direct sun

PRINCIPAL DISPLAY PANEL - 4.25g Stick Carton

Exceptionally
Healthy Lips
Inside & Out

Blistex®